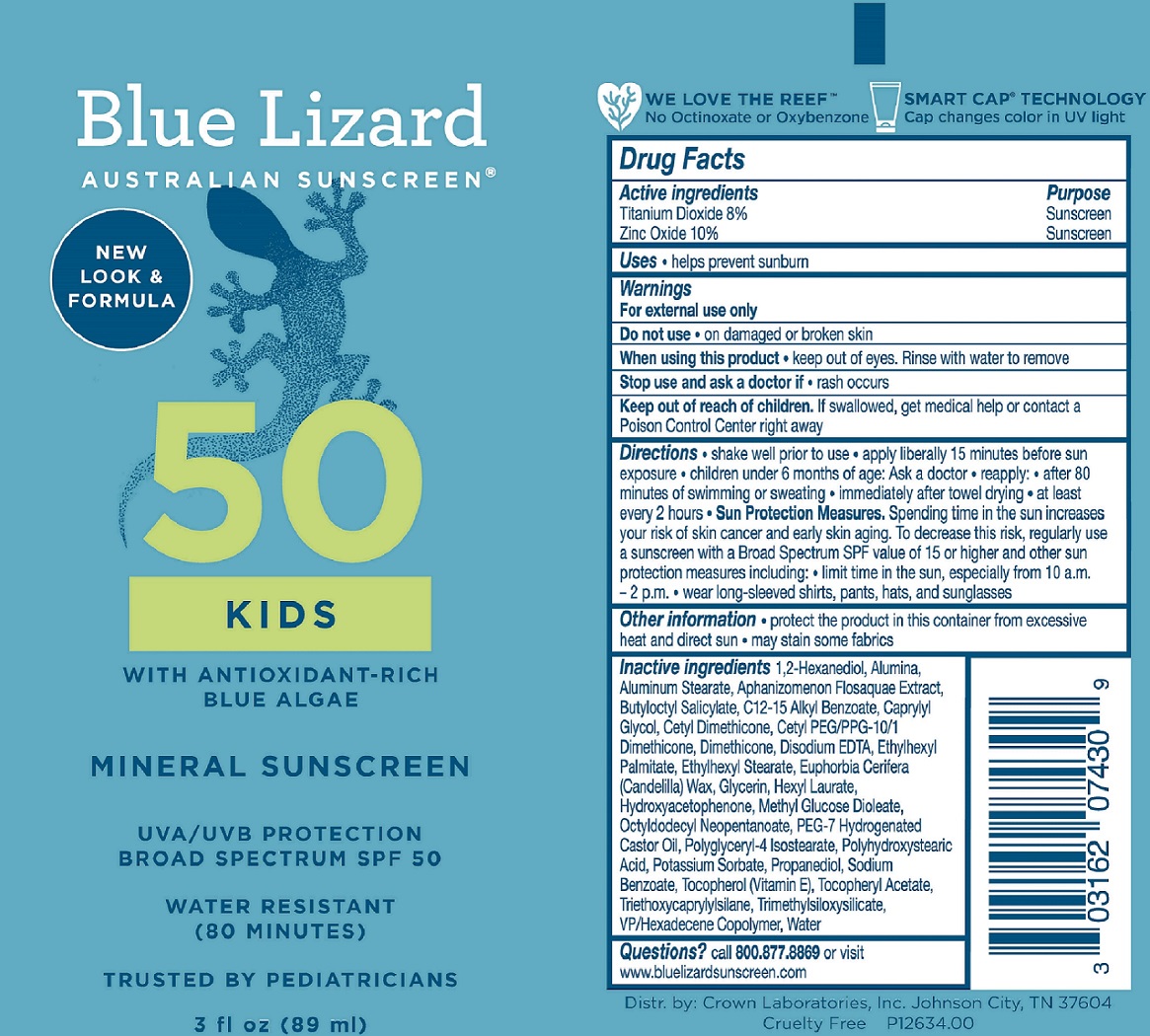 DRUG LABEL: Blue Lizard Kids SPF 50 Sunscreen
NDC: 0316-2074 | Form: LOTION
Manufacturer: Crown Laboratories
Category: otc | Type: HUMAN OTC DRUG LABEL
Date: 20260112

ACTIVE INGREDIENTS: TITANIUM DIOXIDE 90.4 mg/1 mL; ZINC OXIDE 113 mg/1 mL
INACTIVE INGREDIENTS: ALUMINUM OXIDE; ALUMINUM STEARATE; TRIETHOXYCAPRYLYLSILANE; CETYL PEG/PPG-10/1 DIMETHICONE (HLB 5); ALKYL (C12-15) BENZOATE; EDETATE DISODIUM; ETHYLHEXYL PALMITATE; ETHYLHEXYL STEARATE; CAPRYLYL GLYCOL; HEXYL LAURATE; METHYL GLUCOSE DIOLEATE; OCTYLDODECYL NEOPENTANOATE; PEG-7 HYDROGENATED CASTOR OIL; POLYGLYCERYL-4 ISOSTEARATE; PROPANEDIOL; WATER; .ALPHA.-TOCOPHEROL ACETATE; DIMETHICONE; TRIMETHYLSILOXYSILICATE (M/Q 0.8-1.0); HEXADECYL POVIDONE (4 HEXADECYL BRANCHES/REPEAT); POLYHYDROXYSTEARIC ACID (2300 MW); CETYL DIMETHICONE 25; TOCOPHEROL; SODIUM BENZOATE; 1,2-HEXANEDIOL; HYDROXYACETOPHENONE; APHANIZOMENON FLOSAQUAE; BUTYLOCTYL SALICYLATE; EUPHORBIA CERIFERA (CANDELILLA) WAX; POTASSIUM SORBATE; GLYCERIN

Blue Lizard Kids SPF 50 Sunscreen

Active ingredients

Titanium Dioxide 8%

Zinc Oxide 10%

Purpose

Sunscreen

Uses

- helps prevent sunburn

Warnings

For external use only

Do not use • on damaged or broken skin

When using this product • keep out of eyes. Rinse with water to remove

Stop use and ask doctor if • rash occurs

Keep out of reach of children. If swallowed, get medical help or contact a Poison Control Center right away

Directions

• shake well prior to use

• apply liberally 15 minutes before sun exposure

• children under 6 months of age: ask a doctor

• reapply:

• after 80 minutes of swimming or sweating

• immediately after towel drying

• at least every 2 hours

• Sun Protection Measures. Spending time in the sun increases your risk of skin cancer and early skin aging. To decrease this risk, regularly use a sunscreen with a Broad Spectrum SPF value of 15 or higher and other sun protection measures including: • limit time in the sun, especially from 10 a.m. - 2 p.m. • wear long-sleeved shirts, pants, hats, and sunglasses.

Other information

- protect the product in this container from excessive heat and direct sun
- may stain some fabrics

Inactive ingredients

1,2-Hexanediol, Alumina, Aluminum Stearate, Aphanizomenon Flosaquae Extract, Butyloctyl Salicylate, C12-15 Alkyl Benzoate, Caprylyl Glycol, Cetyl Dimethicone, Cetyl PEG/PPG-10/1 Dimethicone, Dimethicone, Disodium EDTA, Ethylhexyl Palmitate, Ethylhexyl Stearate, Euphorbia Cerifera (Candelilla) Wax, Glycerin, Hexyl Laurate, Hydroxyacetophenone, Methyl Glucose Dioleate, Octyldodecyl Neopentanoate, PEG-7 Hydrogenated Castor Oil, Polyglyceryl-4 Isostearate, Polyhydroxystearic Acid, Potassium Sorbate, Propanediol, Sodium Benzoate, Tocopherol (Vitamin E), Tocopheryl Acetate, Triethoxycaprylylsilane, Trimethylsiloxysilicate, VP/Hexadecene Copolymer, Water

Questions?

call 800.877.8869 or visit www.bluelizardsunscreen.com

Blue Lizard Kids 3oz Tube

Blue Lizard

Australian Sunscreen

50

KIDS

with Antioxidant-Rich

Blue Algae

MINERAL SUNSCREEN

UVA/UVB PROTECTION

BROAD SPECTRUM SPF 50

WATER RESISTANT

(80 MINUTES)

TRUSTED BY PEDIATRICIANS

3 fl oz (89 ml)